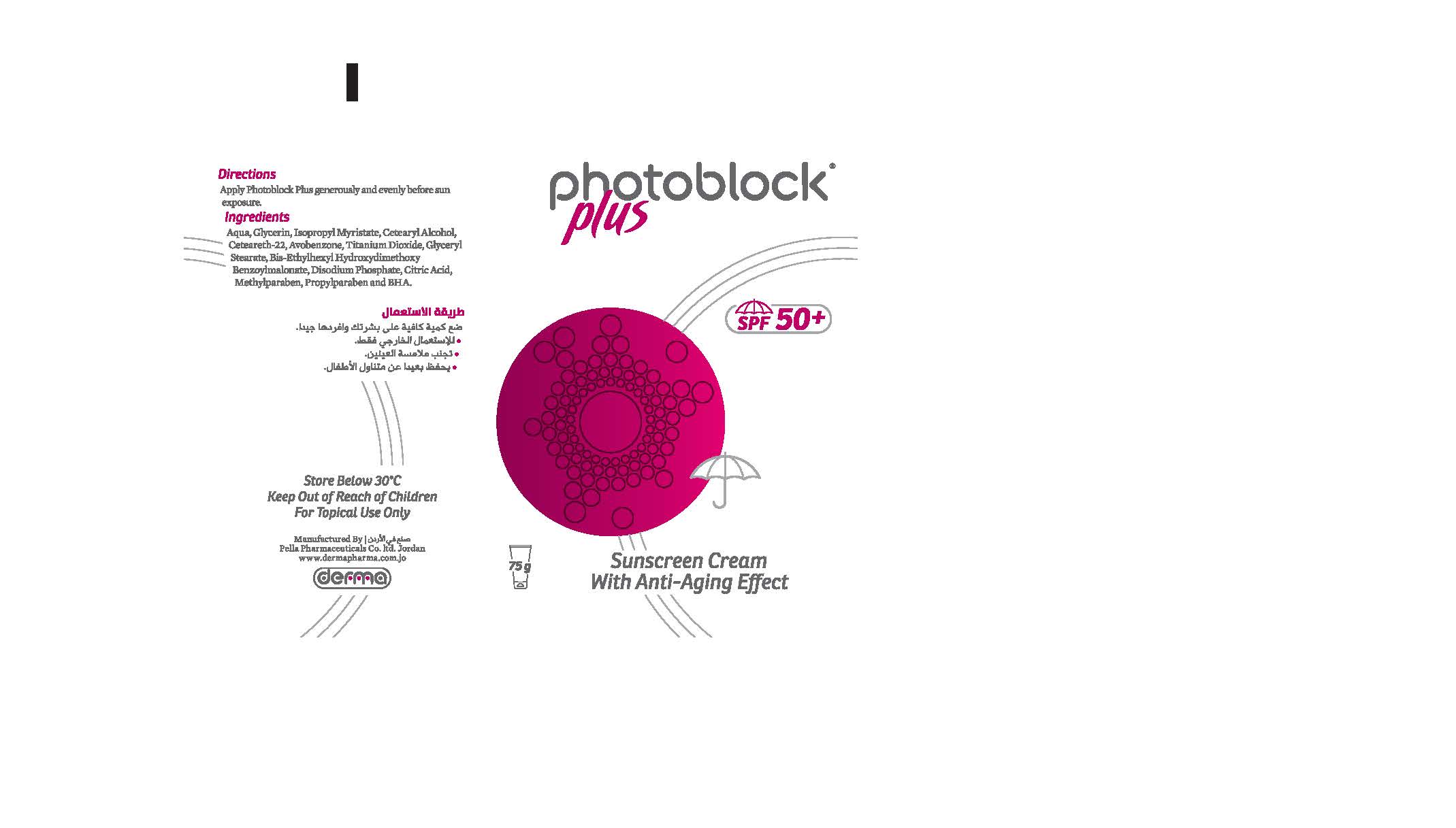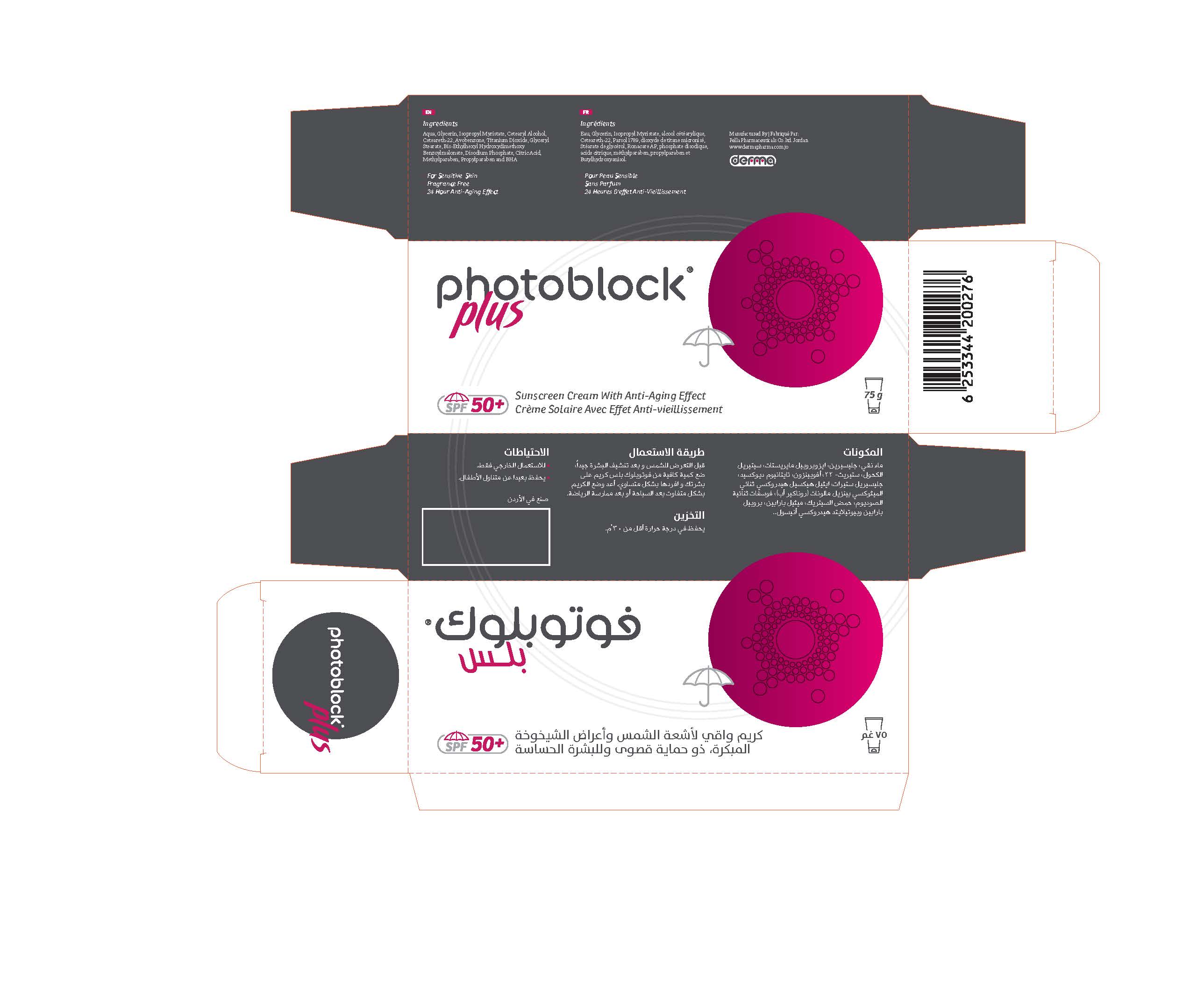 DRUG LABEL: Photoblock Plus
NDC: 82160-276 | Form: CREAM
Manufacturer: Pella Pharmaceuticals Co. Ltd
Category: otc | Type: HUMAN OTC DRUG LABEL
Date: 20211124

ACTIVE INGREDIENTS: AVOBENZONE 22.5 mg/75 g; TITANIUM DIOXIDE 22.5 mg/75 g; BIS-ETHYLHEXYL HYDROXYDIMETHOXY BENZYLMALONATE 7.5 mg/75 g
INACTIVE INGREDIENTS: GLYCERIN; WATER; CETEARETH-22; CETOSTEARYL ALCOHOL; ISOPROPYL MYRISTATE; GLYCERYL MONOSTEARATE; SODIUM PHOSPHATE, DIBASIC; ANHYDROUS CITRIC ACID; METHYLPARABEN; PROPYLPARABEN; BUTYLATED HYDROXYANISOLE

Photoblock Plus

Forms and Presentation

Cream: Tube of 75 g.

Active Ingredients

Avobenzone

Titanium Dioxide

Bis-Ethylhexyl Hydroxydimethoxy Benzylmalonate

Inactive Ingredients

Aqua, Glycerin, Isopropyl Myristate, Cetearyl Alcohol, Ceteareth-22, Glyceryl Stearate, Disodium Phosphate, Citric Acid, Methylparaben, Propylparaben and BHA.

Purpose

Sunscreen

Properties

Photoblock® Plus Cream is a sunscreen and anti-aging cream. which is characterized by its maximum protection SPF 50 + (recognized by global health authorities and scientists) that protects against UVA and UVB.
Photoblock® Plus Cream does not cause acne and will not clog pores. Photoblock® Plus Cream provides sustained protection during peak daytime temperature.

Indications

Photoblock® Plus Cream is used to provide maximum sun protection while maintaining a youthful and radiant skin.
Photoblock® Plus Cream protects the skin against premature aging caused by exposure to UVA due to its components Ronacare AP and Parsol 1789 (A vobenzone), the only substances approved by the American FDA "Food and Drug Administration", which provide complete protection against UVA. It also contains Titanium Dioxide which provides protection against UVB rays that cause redness and burns.

Contraindications

Hypersensitivity to any of the components.

Precautions

- Keep out of reach of children

Warnings

- For external use only
- Avoid conact with eyes

Side effects

Photoblock® Plus Cream has no known side effects, its use is harmless.

Dosage and administration

Apply Photoblock® Plus Cream about 15 minutes before sun exposure. Apply Photoblock® Plus Cream on intact skin, apply a sufficient amount and massage gently.
Reapply every 2 hours or after swimming or sports.

Storage conditions

Store at a temperature below 30 ° C.